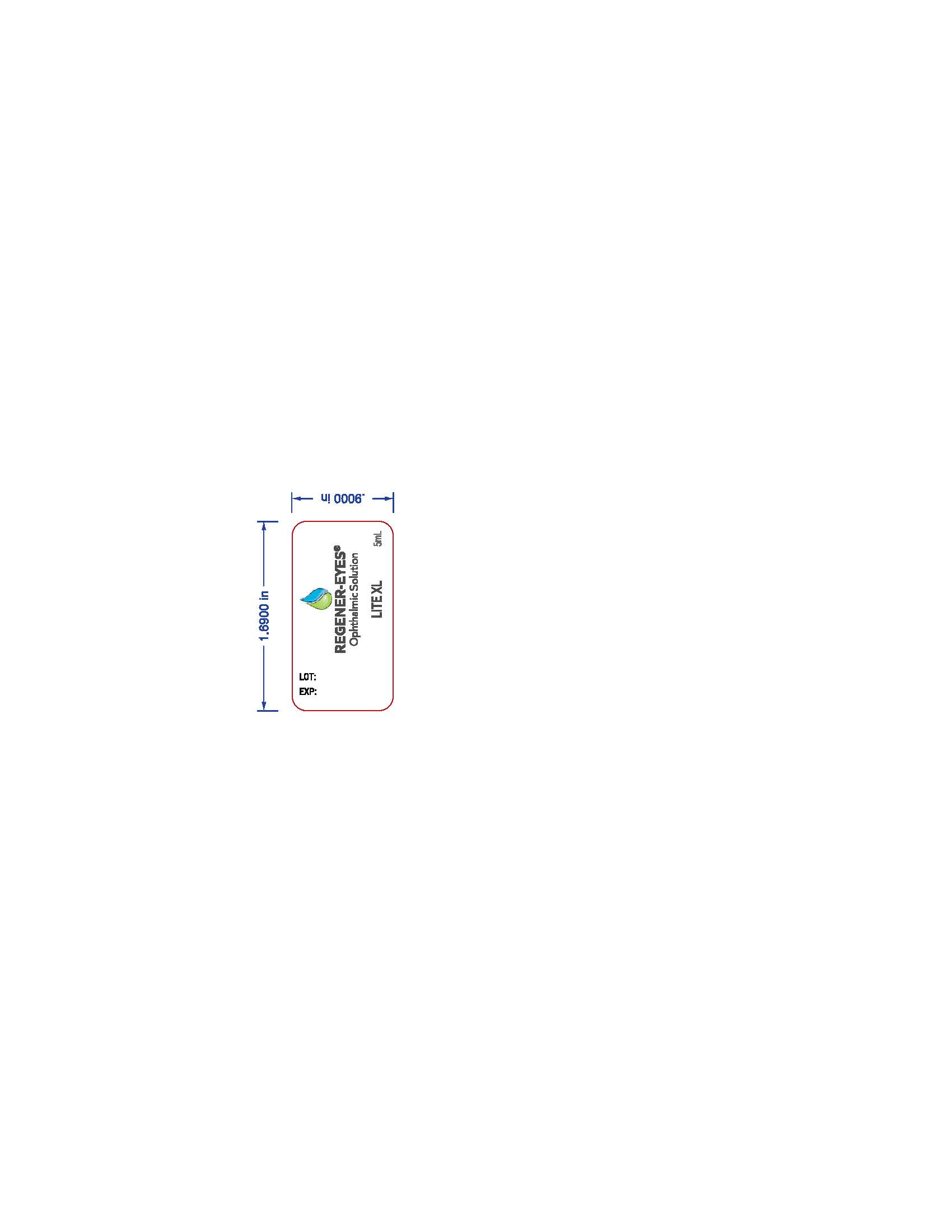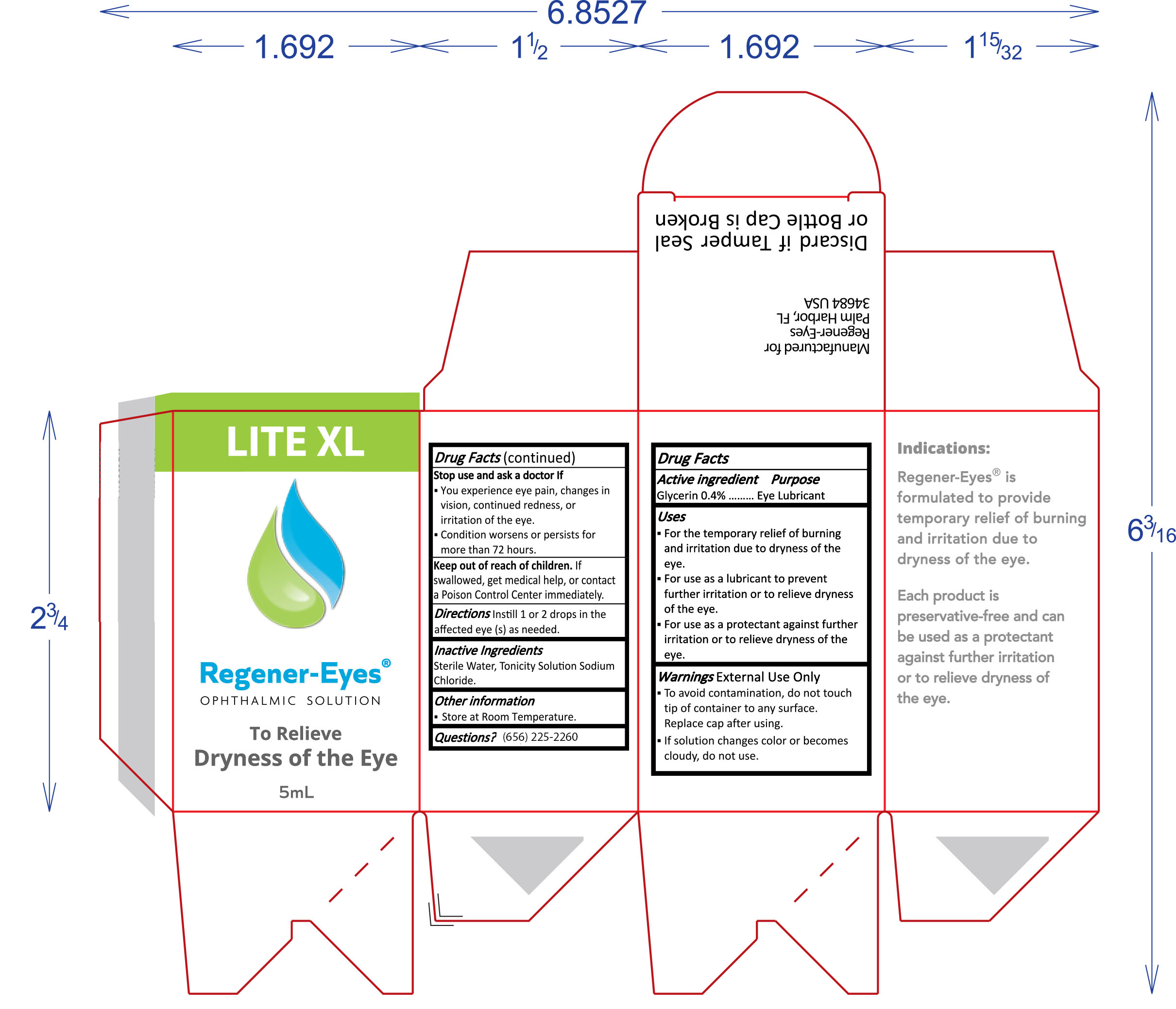 DRUG LABEL: Regener-Eyes Ophthalmic Solution LITE XL
NDC: 87354-001 | Form: SOLUTION/ DROPS
Manufacturer: M & M PRODUCTS, L.L.C.
Category: otc | Type: HUMAN OTC DRUG LABEL
Date: 20260129

ACTIVE INGREDIENTS: GLYCERIN 4 mg/1 mL
INACTIVE INGREDIENTS: WATER; SODIUM CHLORIDE

Carton Labeling - Drug Facts and other Panels (Non-PDP)

Drug Facts
Active ingredient Glycerin 0.4%

Purpose: Eye Lubricant

Uses:
For the temporary relief of burning and irritation due to dryness of the eye. For use as a lubricant to prevent further irritation or to relieve dryness of the eye. For use as a protectant against further irritation or to relieve dryness of the eye.

Warnings:
External Use Only. To avoid contamination, do not touch tip of container to any surface. Replace cap after using. If solution changes color or becomes cloudy, do not use.
Stop use and ask a doctor If:
You experience eye pain, changes in vision, continued redness, or irritation of the eye. Condition worsens or persists for more than 72 hours.
Keep out of reach of children
If swallowed, get medical help, or contact a Poison Control Center immediately.

Directions
Instill 1 or 2 drops in the affected eye (s) as needed.

Inactive Ingredients
Sterile Water, Tonicity Solution Sodium Chloride.

Other information
Store at Room Temperature.

Questions?
(656) 225-2260

Indications
Regener-Eyes® is formulated to provide temporary relief of burning and irritation due to dryness of the eye. Each product is preservative-free and can be used as a protectant against further irritation or to relieve dryness of the eye.

Active Ingredient

Active ingredient Glycerin 0.4%

Purpose

Purpose: Eye Lubricant

Warnings

External Use Only. To avoid contamination, do not touch tip of container to any surface. Replace cap after using. If solution changes color or becomes cloudy, do not use.

Stop use and ask a doctor If:
You experience eye pain, changes in vision, continued redness, or irritation of the eye. Condition worsens or persists for more than 72 hours.

Keep out of reach of children
If swallowed, get medical help, or contact a Poison Control Center immediately.

Indications and Uses

Uses:
For the temporary relief of burning and irritation due to dryness of the eye. For use as a lubricant to prevent further irritation or to relieve dryness of the eye. For use as a protectant against further irritation or to relieve dryness of the eye.

Indications
Regener-Eyes® is formulated to provide temporary relief of burning and irritation due to dryness of the eye. Each product is preservative-free and can be used as a protectant against further irritation or to relieve dryness of the eye.

Dosage and Administration

Directions
Instill 1 or 2 drops in the affected eye (s) as needed.

Inactive Ingredients

Sterile Water, Tonicity Solution Sodium Chloride.

When Using

Store at Room Temperature.

Patient Counseling

Questions?
(656) 225-2260

Keep out of reach of Children

If swallowed, get medical help, or contact a Poison Control Center immediately.

Carton PDP - Front Panel - 5mL

Proprietary Name: Regener-Eyes Ophthalmic Solutiion LITE XL

Product Descriptor: Eye Lubricant

Key Claims: To Relieve Dryness of the Eye

Net Contents: 5mL